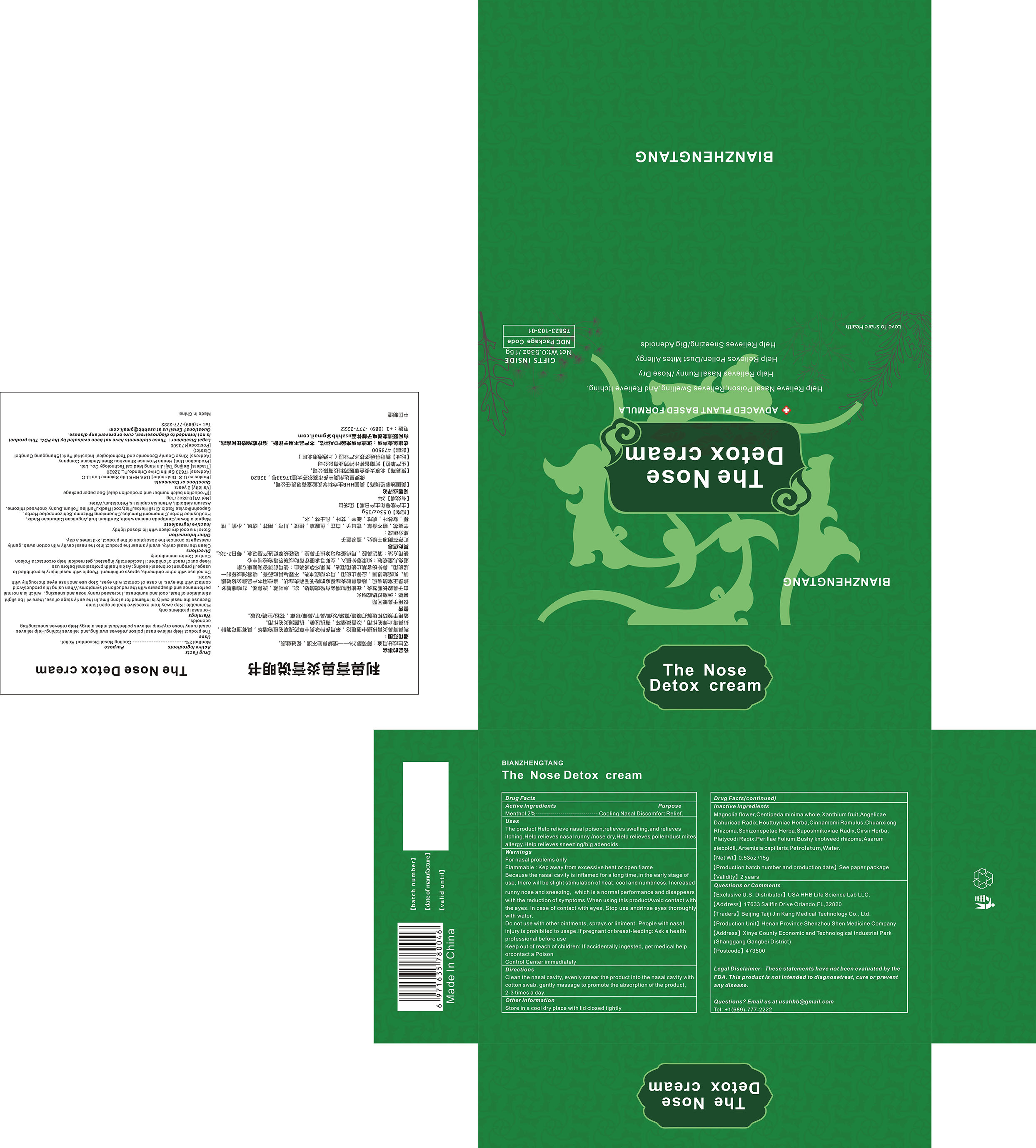 DRUG LABEL: The Nose Detox cream
NDC: 75823-103 | Form: CREAM
Manufacturer: Beijing Taiji Jin Kang Medical Technology Co., Ltd.
Category: otc | Type: HUMAN OTC DRUG LABEL
Date: 20200820

ACTIVE INGREDIENTS: MENTHOL 2 g/100 g
INACTIVE INGREDIENTS: PERILLA FRUTESCENS LEAF; MAGNOLIA SPRENGERI FLOWER BUD; CENTIPEDA MINIMA WHOLE; XANTHIUM SIBIRICUM FRUIT; ANGELICA DAHURICA ROOT; POLYGONUM CUSPIDATUM ROOT; CINNAMOMUM CASSIA TWIG; LIGUSTICUM WALLICHII ROOT; SCHIZONEPETA TENUFOLIA SPIKE; SAPOSHNIKOVIA DIVARICATA ROOT; CIRSIUM ARVENSE FLOWERING TOP; PLATYCODON GRANDIFLORUM ROOT; HOUTTUYNIA CORDATA TOP; PETROLATUM; ASARUM SIEBOLDII; ARTEMISIA CAPILLARIS LEAF; WATER

103 The Nose Detox cream

ACTIVE INGREDIENT

Menthol

Health Care

cooling Nasal discomfort relief

Appropriate Crowd

The product Help relieve nasal poison,relieves swelling,and relieves itching.Help relieves nasal runny /nose dry,Help relieves pollen/dust mites allergy.Help relieves sneezing/big adenoids.

Unsuitable Crowd

Do not use with other ointments, sprays or liniment. People with nasal injury is prohibited to usage. If pregnant or breast-leeding: Ask a health professional before use

Directions

Clean the nasal cavity, apply this product evenly in the nasal cavity, gently massage to help the absorption of this product. Use 2-3 times a day.

Precautions for use

For nasal problems only
Flammable: Kep away from excessive heat or open flame

Because the nasal cavity is inflamed for a long time, In the early stage of use, there will be slight stimulation of heat, cool and numbess, Increased runny nose and sneezing, which is a normal performance and disappears with the reduction of symptoms.

Storage

Store in a cool dry place with lid closed tightly

When using this productAvoid contact with the eyes.

STOP USE

In case of contact with eyes, Stop use andrinse eyes thoroughly with water.

Keep out of reach of children: If accidentally ingested, get medical help orcontact a Poison Control Center immediately

Inactive ingredients

Magnolia flower, Centipeda minima whole, Xanthium fruit, Angelicae Dahuricae Radix, Houttuyniae Herba, Cinnamomi Ramulus,Chuanxiong Rhizoma, Schizonepetae Herba, Saposhnikoviae Radix, Cirsii Herba, Platycodi Radix, Perillae Folium, Bushy knotweed rhizome, Asarum sieboldll, Artemisia capillaris, PETROLATUM, Water